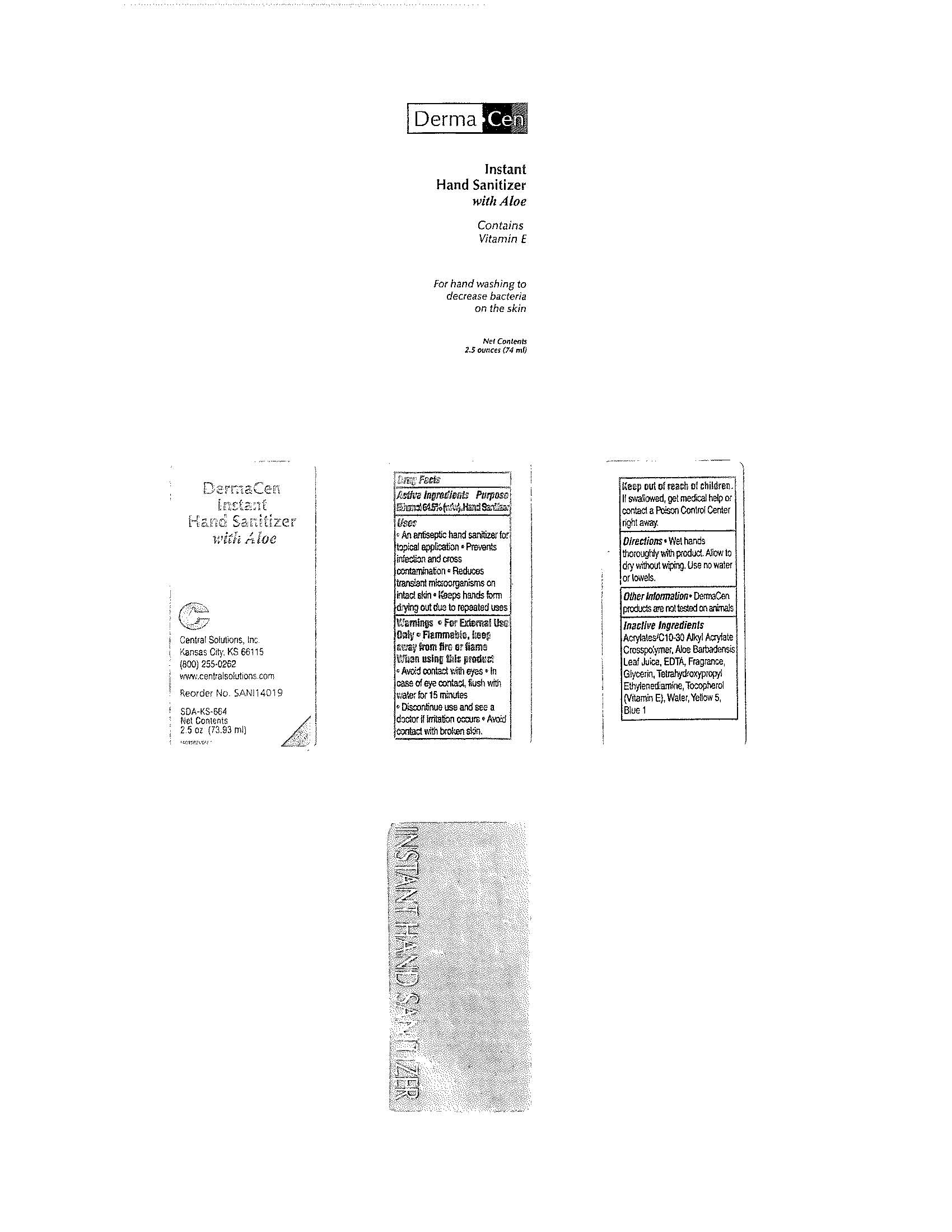 DRUG LABEL: DermaCen Instant Hand Sanitizer with Aloe
NDC: 62654-143 | Form: LIQUID
Manufacturer: Central Solutions Inc
Category: otc | Type: HUMAN OTC DRUG LABEL
Date: 20241209

ACTIVE INGREDIENTS: ALCOHOL 64.5 mL/100 mL
INACTIVE INGREDIENTS: CARBOMER INTERPOLYMER TYPE A (ALLYL SUCROSE CROSSLINKED); ALOE VERA LEAF; EDETIC ACID; GLYCERIN; EDETOL; TOCOPHEROL; WATER; FD&C YELLOW NO. 5; FD&C BLUE NO. 1

Drug Facts 62654-143

Active Ingredients

Ethanol 64.5% (w/w)

Purpose

Hand Sanitizer

Uses

An antiseptic hand sanitizer for topical application

Prevents infection and cross contamination

Reduces transient microorganisms on intact skin

Keeps hands from drying out due to repeated uses

Warnings

For External Use Only

Flammable, keep away from fire or flame

When using this product

Avoid contact with eyes

In case of eye contact, flush with water for 15 minutes

Discontinue use and see a doctor if irritation occurs

Avoid contact with broken skin.

Keep out of reach of children.

If swallowed, get medical help or contact a Poison Control Center right away.

Directions

Wet hands thoroughly with product.

Allow to dry without wiping.

Use no water or towels.

Other Information

DermaCen products are not tested on animals

Inactive Ingredients

Acrylates/C10-30 Alkyl Acrylate Crosspolymer, Aloe Barbadensis Leaf Juice, EDTA, Fragrance, Glycerin, Tetrahydroxypropyl Ethylenediamine, Tocopherol (Vitamin E), Water, Yellow 5, Blue 1

PACKAGE LABEL

DermaCen

Instant

Hand Sanitizer

with Aloe

Contains

Vitamin E

For hand washing

to decrease bacteria

on the skin

Net Contents

2.5 ounces (74 ml)